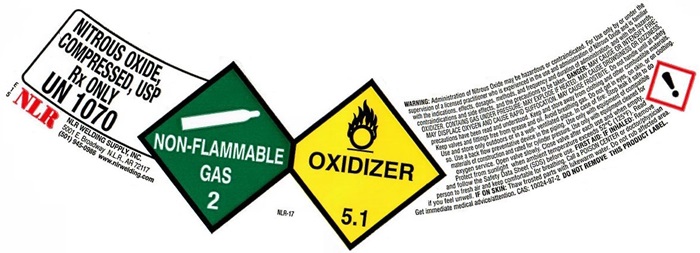 DRUG LABEL: NITROUS OXIDE
NDC: 62045-8333 | Form: GAS
Manufacturer: NLR Welding Supply, Inc.
Category: prescription | Type: HUMAN PRESCRIPTION DRUG LABEL
Date: 20231108

ACTIVE INGREDIENTS: NITROUS OXIDE 99 L/100 L

Nitrous Oxide

NITROUS OXIDE USP LABEL

NITROUS OXIDE, COMPRESSED, USP Rx ONLY UN1070

NLR NLR WELDING SUPPLY, INC.

5001 E. Broadway N.L.R., AR 72117

(501) 945-0986 www.nlrwelding.com

NON-FLAMMABLE GAS 2 OXIDIZER 5.1

NLR-17

WARNING: Administration of Nitrous Oxide may be hazardous or contraindicated. For use only by or under supervision of a licensed practitioner who is experienced in the use and administration of Nitrous Oxide and is familiar with the indications, effects, dosages, methods, and frequency and duration of administration, and with the hazards, contraindications, and side effects and the precautions to be taken. DANGER: HIGH PRESSURE OXIDIZING LIQUID AND GAS. VIGOROUSLY ACCELERATES COMBUSTION. CAN CAUSE RAPID SUFFOCATION. CAN CAUSE ANESTHETIC EFFECTS. MAY CAUSE FROSTBITE. Do not handle until all safety precautions have been read and understood. Keep and store away from clothing and other combustible materials. Keep valves and fittings fitting free from grease and oil. Avoid breathing gas. Do not get in eyes, on skin, or on clothing. Use and store outdoors or in a well-ventilated place. In case of fire: Stop leak if safe to do so. Use a backflow preventative device in the piping. Use only with equipment of compatible materials of construction and rated for cylinder pressure. Use only with equipment cleaned for oxygen service. Open valve slowly. Close valve after each use and when empty. Protect from sunlight when ambient temperature exceeds 52°C (125°F). Read and follow the Safety Data Sheet (SDS) before use. FIRST AID: IF INHALED: Remove person to fresh air and keep comfortable for breathing. Call a POISON CENTER or doctor/physician if you feel unwell. IF ON SKIN: Thaw frosted parts with lukewarm water. Do not rub affected area. Get immediate medical advice/attention. CAS: 10024-97-2 DO NOT REMOVE THIS PRODUCT LABEL